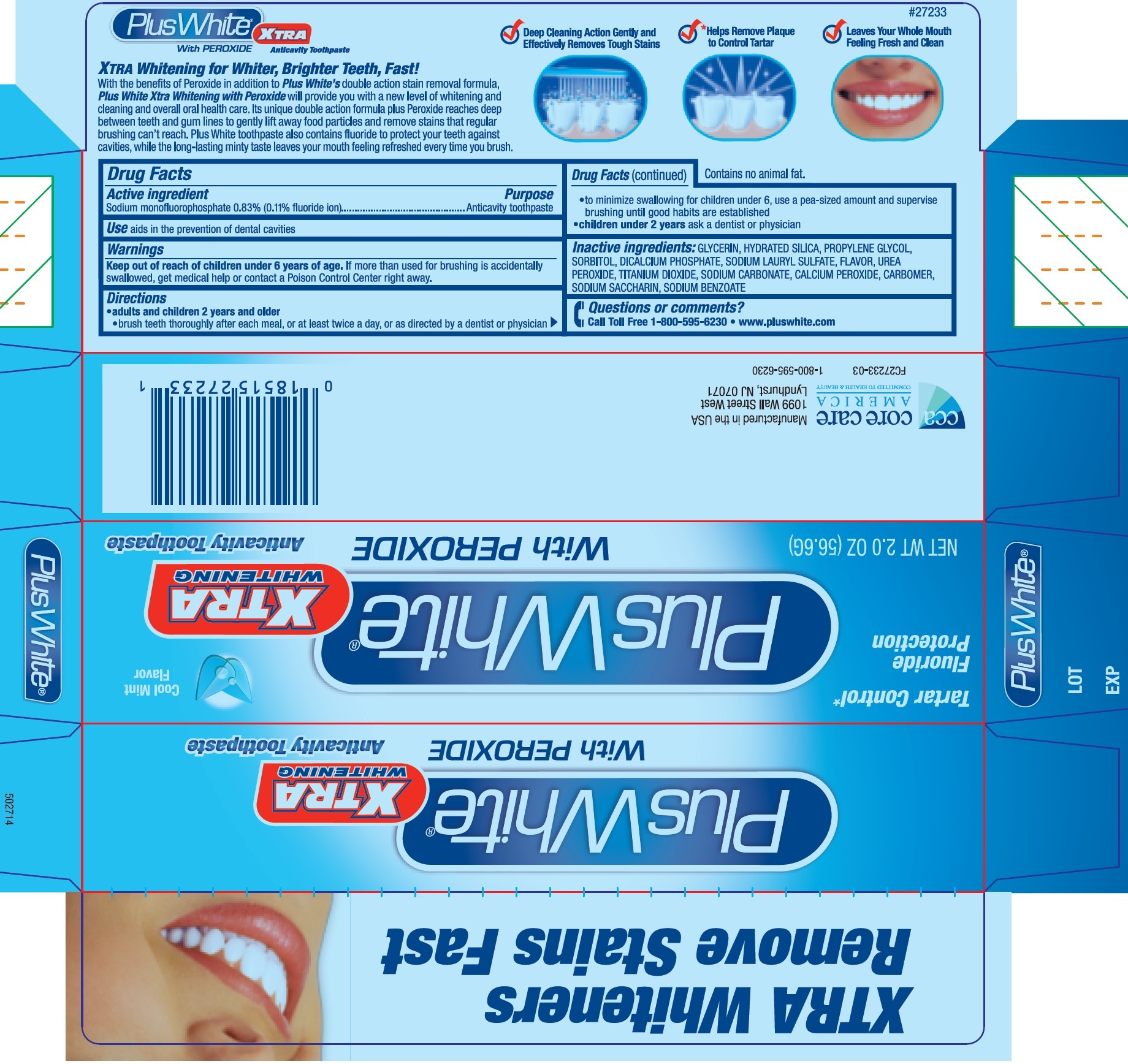 DRUG LABEL: Plus White With Peroxide
NDC: 61543-7233 | Form: PASTE
Manufacturer: CCA Industries, Inc.
Category: otc | Type: HUMAN OTC DRUG LABEL
Date: 20200923

ACTIVE INGREDIENTS: SODIUM MONOFLUOROPHOSPHATE 1.5 mg/1 g
INACTIVE INGREDIENTS: GLYCERIN; HYDRATED SILICA; PROPYLENE GLYCOL; SORBITOL; ANHYDROUS DIBASIC CALCIUM PHOSPHATE; SODIUM LAURYL SULFATE; METHYL SALICYLATE; CARBAMIDE PEROXIDE; TITANIUM DIOXIDE; SACCHARIN SODIUM; SODIUM CARBONATE; CALCIUM PEROXIDE; CARBOXYPOLYMETHYLENE; SODIUM BENZOATE

Plus White With Peroxide

Active ingredient

Sodium Monofluorophosphate 0.83% (0.11% w/v fluoride ion)

Purpose

Anticavity whitening toothpaste

Use

aids in the prevention of dental cavities

Warnings

Keep out of reach of children under 6 years of age

If more than used for brushing is accidentally swallowed, get medical help or contact a Poison Control Center right away.

Directions

- adults and children 2 years and older
- b rush teeth thoroughly after each meal, or at least twice a day, or as directed by a dentist or physician
- to minimize swallowing for children under 6, use a pea-sized amount and supervise brushing until good habits are established
- children under 2 years, ask a dentist or physician.

Inactive ingredients:

GLYCERIN, HYDRATED SILICA, PROPYLENE GLYCOL, SORBITOL, DICALCIUM PHOSPHATE, SODIUM LAURYL SULFATE, FLAVOR, UREA PEROXIDE, TITANIUM DIOXIDE, SODIUM CARBONATE, CALCIUM PEROXIDE, CARBOMER, SODIUM SACCHARIN, SODIUM BENZOATE.

Questions or comments?

call Toll Free 1-800-595-6230 • www.pluswhite.com